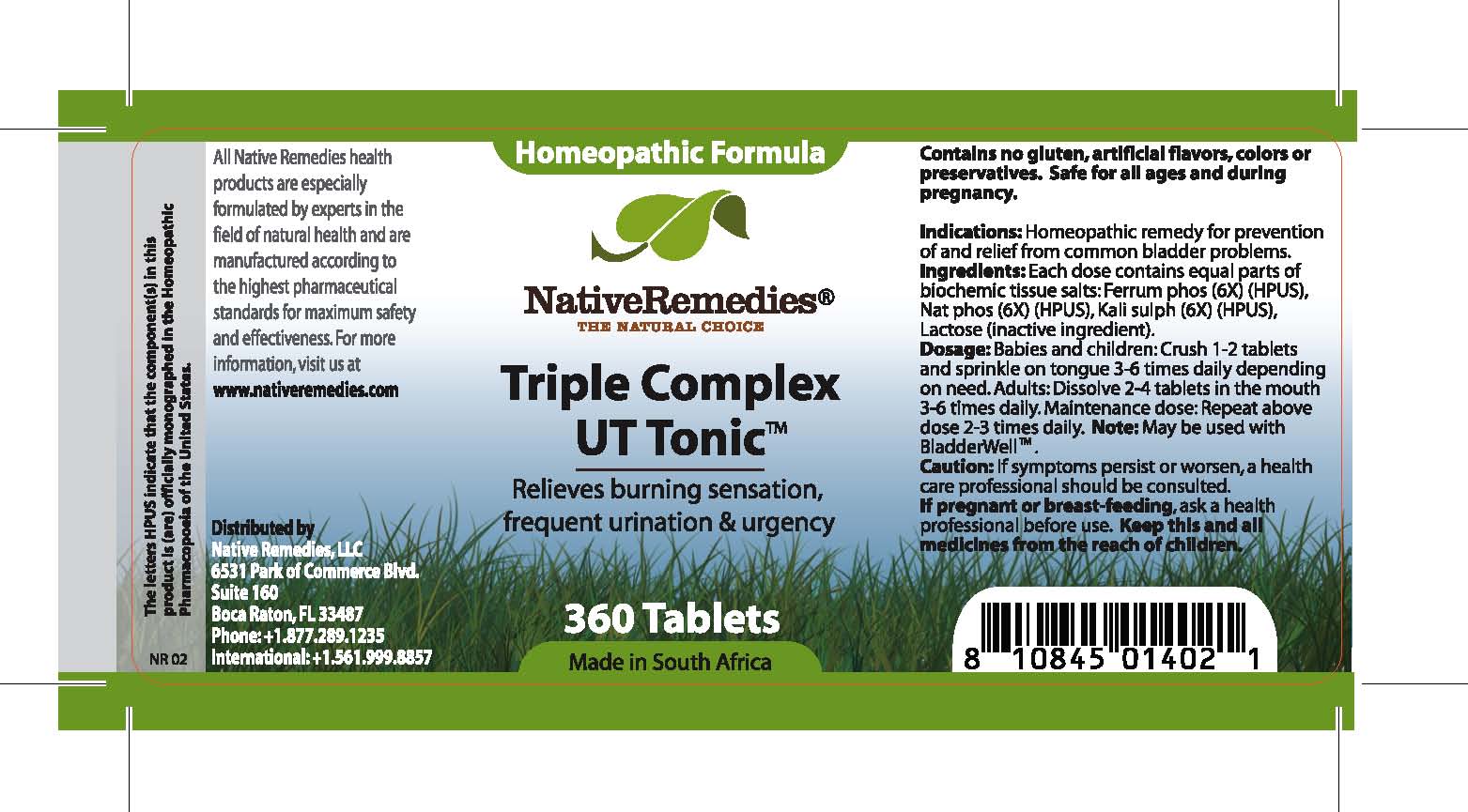 DRUG LABEL: Triple Complex UT Tonic
								
NDC: 68647-133 | Form: TABLET
Manufacturer: Feelgood Health
Category: homeopathic | Type: HUMAN OTC DRUG LABEL
Date: 20100902

ACTIVE INGREDIENTS: FERRUM PHOSPHORICUM 6 [hp_X]/1 1; SODIUM PHOSPHATE, DIBASIC ANHYDROUS 6 [hp_X]/1 1; POTASSIUM SULFATE 6 [hp_X]/1 1
INACTIVE INGREDIENTS: LACTOSE

TRIPLE COMPLEX UT TONIC

PURPOSE

Relieves burning sensation, frequent urination and urgency

INDICATIONS AND USAGE

Indications: Homeopathic remedy for prevention of and relief from common bladder problems.

DOSAGE AND ADMINISTRATION

Dosage: Babies and children: Crush 1-2 tablets and sprinkle on tongue 3-6 times daily depending on need. Adults: Dissolve 2-4 tablets in the mouth 3-6 times daily. Maintenance dose: Repeat above dose 2-3 times daily. May be used with BladderWell .

GENERAL PRECAUTIONS

Dosage: Babies and children: Crush 1-2 tablets and sprinkle on tongue 3-6 times daily depending on need. Adults: Dissolve 2-4 tablets in the mouth 3-6 times daily. Maintenance dose: Repeat above dose 2-3 times daily. May be used with BladderWell .

ACTIVE INGREDIENT

Ingredients: Each dose contains equal parts of biochemic tissue salts: Ferrum phos (6X) (HPUS), Nat phos (6X) (HPUS), Kali sulph (6X) (HPUS)

Lactose (inactive ingredient).

PREGNANCY

If pregnant or breastfeeding, ask a health professional before use.

WARNINGS

Contains no gluten, artificial flavors, colors or preservatives.Safe for all ages and during pregnancy.

PATIENT COUNSELING INFORMATION

All Native Remedies health products are especially formulated by experts in the field of natural health and are manufactured according to the highest pharmaceutical standards for maximum safety and effectiveness. For more information, visit us at www.nativeremedies.com

Distributed by

Native Remedies, LLC

6531 Park of Commerce Blvd.

Suite 160

Boca Raton, FL 33487

Phone: 1.877.289.1235

International: + 1.561.999.8857

The letters HPUS indicate that the component(s) in this product is (are) officially monographed in the Homeopathic Pharmacopoeia of the United States.

KEEP OUT OF REACH OF CHILDREN

Keep this and all medicines from the reach of children.